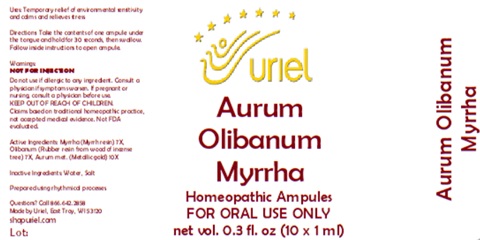 DRUG LABEL: Aurum Olibanum Myrrha
NDC: 48951-1196 | Form: LIQUID
Manufacturer: Uriel Pharmacy Inc.
Category: homeopathic | Type: HUMAN OTC DRUG LABEL
Date: 20260225

ACTIVE INGREDIENTS: MYRRH 7 [hp_X]/1 mL; FRANKINCENSE 7 [hp_X]/1 mL; GOLD 10 [hp_X]/1 mL
INACTIVE INGREDIENTS: WATER; SODIUM CHLORIDE

Aurum Olibanum Myrrha

PURPOSE

Uses: Temporary relief of environmental sensitivity and calms and relieves stress.

INDICATIONS AND USAGE

FOR ORAL USE ONLY

DOSAGE AND ADMINISTRATION

Directions: Take the contents of one ampule under the tongue and hold for 30 seconds, then swallow. Follow inside instructions to open ampule.

Warnings:
NOT FOR INJECTION
Do not use if allergic to any ingredient. Consult a physician if symptoms worsen. If pregnant or nursing, consult a physician before use.
Claims based on traditional homeopathic practice, not accepted medical evidence. Not FDA evaluated.

KEEP OUT OF REACH OF CHILDREN.

ACTIVE INGREDIENT

Active Ingredients: Myrrha (Myrrh resin) 7X, Olibanum (Rubber resin from wood of incense tree) 7X, Aurum met. (Metallic gold) 10X

Inactive Ingredients: Water, Salt

Prepared using rhythmical processes.

QUESTIONS

Questions? Call 866.642.2858 Made by Uriel, East Troy, WI 53120 shopuriel.com

Lot: